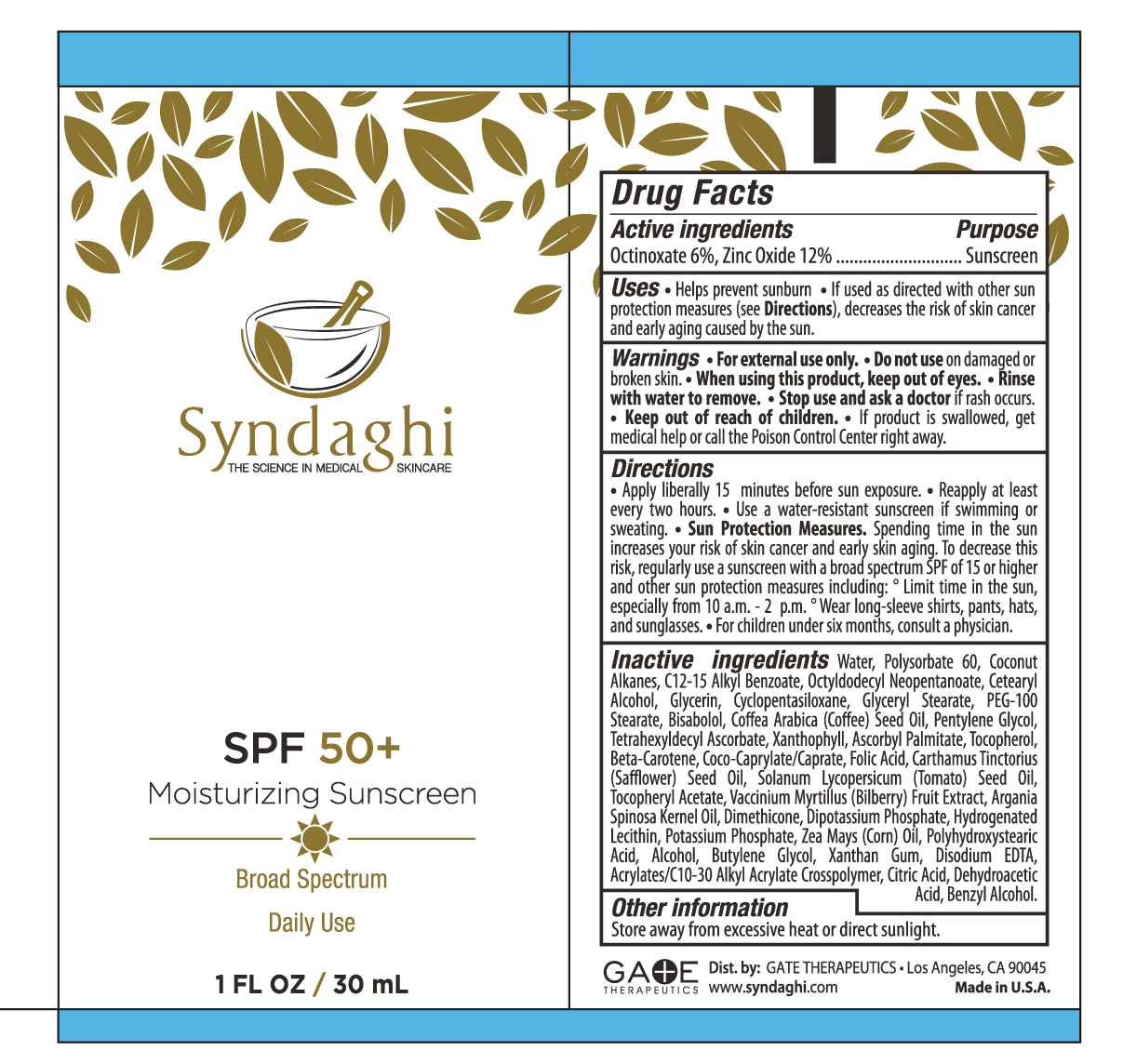 DRUG LABEL: SPF 50 Moisturizing Sunscreen Broad Spectrum
NDC: 72274-002 | Form: LOTION
Manufacturer: GATE THERAPEUTICS
Category: otc | Type: HUMAN OTC DRUG LABEL
Date: 20221130

ACTIVE INGREDIENTS: OCTINOXATE 6 g/100 mL; ZINC OXIDE 12 g/100 mL
INACTIVE INGREDIENTS: WATER; POLYSORBATE 60; COCONUT ALKANES; ALKYL (C12-15) BENZOATE; OCTYLDODECYL NEOPENTANOATE; CETOSTEARYL ALCOHOL; GLYCERIN; CYCLOMETHICONE 5; GLYCERYL MONOSTEARATE; PEG-100 STEARATE; LEVOMENOL; ARABICA COFFEE OIL; PENTYLENE GLYCOL; TETRAHEXYLDECYL ASCORBATE; LUTEIN; ASCORBYL PALMITATE; TOCOPHEROL; .BETA.-CAROTENE; COCO-CAPRYLATE/CAPRATE; FOLIC ACID; SAFFLOWER OIL; TOMATO SEED OIL; .ALPHA.-TOCOPHEROL ACETATE; BILBERRY; ARGAN OIL; DIMETHICONE; DIBASIC POTASSIUM PHOSPHATE; HYDROGENATED SOYBEAN LECITHIN; POTASSIUM PHOSPHATE, MONOBASIC; CORN OIL; POLYHYDROXYSTEARIC ACID (2300 MW); ALCOHOL; BUTYLENE GLYCOL; XANTHAN GUM; EDETATE DISODIUM; CITRIC ACID MONOHYDRATE; DEHYDROACETIC ACID; BENZYL ALCOHOL

SPF 50 Moisturizing Sunscreen

Active Ingredients Purpose

Octinoxate 6%, Zinc Oxide 12% Sunscreen

Uses
• Helps prevent sunburn
• If used as directed with other sun protection measures (see Directions), decreases the risk of skin cancer and early skin aging caused by the sun.

Keep out of reach of children. If Product is swallowed, get medical help or contact a Poison Control Center right away.

Stop use and ask a doctor if rash occurs

Warnings
For External Use Only
Do not use on damaged or broken skin
When using this product keep out of eyes. Rinse with water to remove.

Directions
• Apply liberally 15 minutes before sun exposure

• Reapplyat least every 2 hours
• Use a water resistant sunscreen if swimming or sweating
• Sun Protection Measures. Spending time in the sun increases your risk of skin cancer and early skin aging. To decrease this risk, regularly use a sunscreen with a Broad Spectrum SPF value 15 or higher and other sun protection measures including:
• Limit time in the sun, especially from 10a.m. – 2p.m.
• Wear long-sleeve shirts, pants, hats, and sunglasses
• Children under six months consult a physician

INACTIVE INGREDIENT

Inactive ingredients Water, Polysorbate 60, Coconut Alkanes, C12-15 Alkyl Benzoate, Octyldodecyl Neopentanoate, Cetearyl Alcohol, Glycerin, Cyclopentasiloxane, Glyceryl Stearate, PEG-100 Stearate, Bisabolol, Coffea Arabica (Coffee) Seed Oil, Pentylene Glycol, Tetrahexyldecyl Ascorbate, Xanthophyll, Ascorbyl Palmitate, Tocopherol, Beta-Carotene, Coco-Caprylate/Caprate, Folic Acid, Carthamus Tinctorius (Saffower) Seed Oil, Solanum Lycopersicum (Tomato) Seed Oil, Tocopheryl Acetate, Vaccinium Myrtillus (Bilberry) Fruit Extract, Argania Spinosa Kernel Oil, Dimethicone, Dipotassium Phosphate, Hydrogenated Lecithin, Potassium Phosphate, Zea Mays (Corn) Oil, Polyhydroxystearic Acid, Alcohol, Butylene Glycol, Xanthan Gum, Disodium EDTA, Acrylates/C10-30 Alkyl Acrylate Crosspolymer, Citric Acid, Dehydroacetic Acid, Benzyl Alcohol

PACKAGE LABEL

SPF 50+

Moisturizing Sunscreen

Broad Spectrum Daily Use

1Fl Oz/30 mL